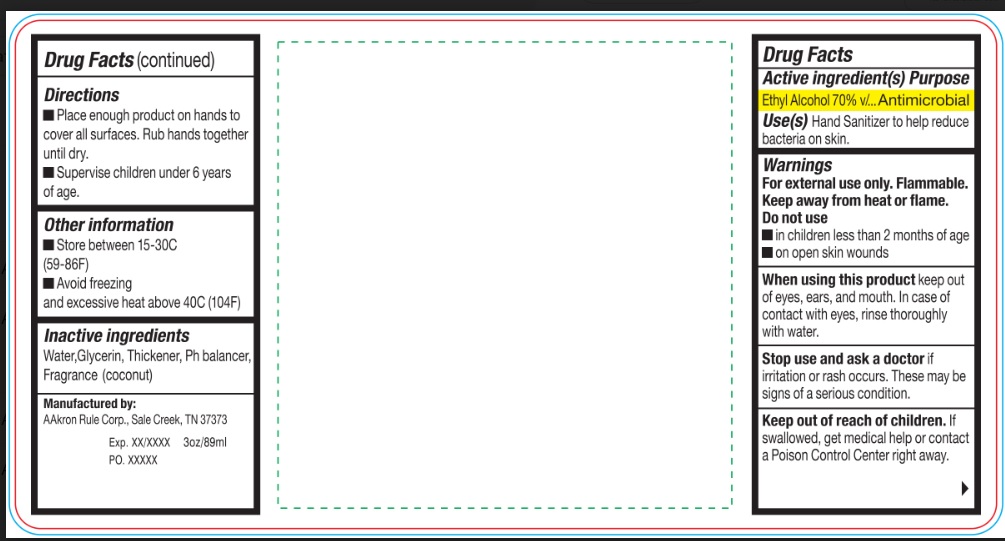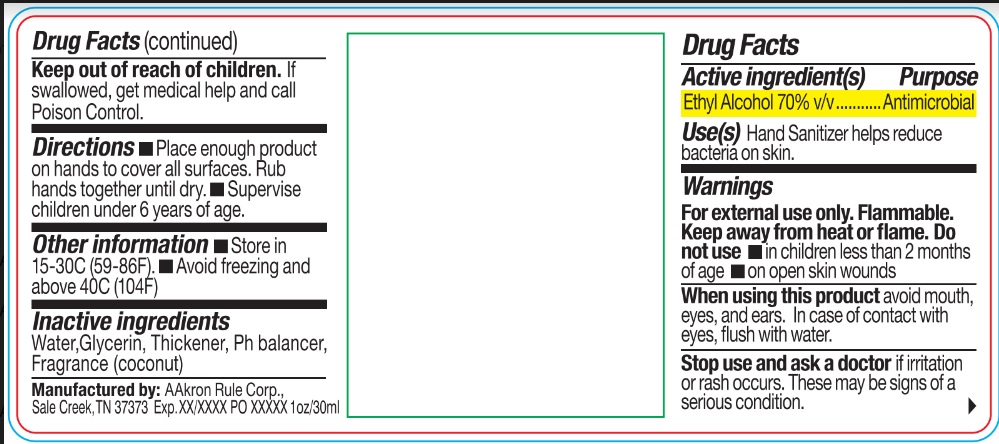 DRUG LABEL: Gel Sanitizer
NDC: 69394-004 | Form: GEL
Manufacturer: AAkron Rule Corporation
Category: otc | Type: HUMAN OTC DRUG LABEL
Date: 20220726

ACTIVE INGREDIENTS: ALCOHOL 70 mL/100 mL
INACTIVE INGREDIENTS: ALOE VERA LEAF; CARBOMER HOMOPOLYMER TYPE C (ALLYL PENTAERYTHRITOL CROSSLINKED); D&C GREEN NO. 5; D&C YELLOW NO. 10; WATER; TROLAMINE

Active Ingredient

Ethyl Alcohol 70% v/v

Purpose

Antimicrobial

Use

Hand Sanitizer to help reduce bacteria on skin.

Warnings

For external use only.

Flammable. Keep away from heat or flame.

Do not use
• In children less than 2 months of age
• On open skin wounds

When using this product avoid mouth, eyes, and ears. In case of contact with eyes, flush with water.

Stop use and ask a doctor if irritation or rash occurs. These may be signs of a serious condition.

Keep out of reach of children. If swallowed, get medical help and call Poison Control.

Directions

- Place enough product on hands to cover all surfaces. Rub hands together until dry.
- Supervise children under 6 years of age.

Other information

- Store in 15-30C (59-86F)
- Avoid freezing and excessive heat above 40C (104F)

Inactive ingredients

Aloe Vera, Carbomer, D&C Green #5, D&C Yellow #10, Water, Trolamine